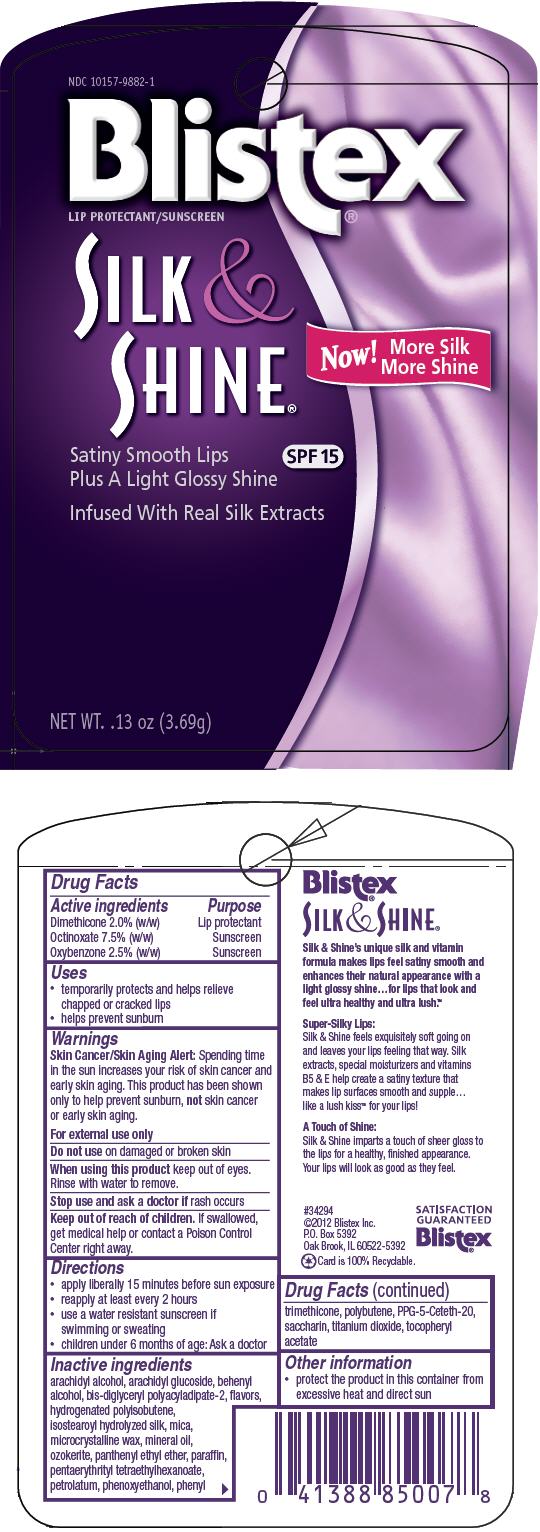 DRUG LABEL: Silk and Shine
NDC: 10157-9882 | Form: STICK
Manufacturer: Blistex Inc
Category: otc | Type: HUMAN OTC DRUG LABEL
Date: 20121017

ACTIVE INGREDIENTS: Dimethicone 2 g/100 g; Octinoxate 7.5 g/100 g; Oxybenzone 2.5 g/100 g
INACTIVE INGREDIENTS: arachidyl alcohol; arachidyl glucoside; docosanol; mica; microcrystalline wax; mineral oil; panthenyl ethyl ether; paraffin; pentaerythrityl tetraethylhexanoate; petrolatum; phenoxyethanol; phenyl trimethicone; PPG-5-Ceteth-20; saccharin; titanium dioxide; isopropyl behenate; Ceresin; Polybutene (1400 MW); Silk, Acid Hydrolyzed (1000 MW); .alpha.-tocopherol acetate

Silk & Shine

Drug Facts

ACTIVE INGREDIENT

Active ingredients | Purpose
Dimethicone 2.0% (w/w) | Lip protectant
Octinoxate 7.5% (w/w) | Sunscreen
Oxybenzone 2.5% (w/w) | Sunscreen

Uses

- temporarily protects and helps relieve chapped or cracked lips
- helps prevent sunburn

Warnings

Skin Cancer/Skin Aging Alert

Spending time in the sun increases your risk of skin cancer and early skin aging. This product has been shown only to help prevent sunburn, not skin cancer or early skin aging.

For external use only

Do not use on damaged or broken skin

When using this product keep out of eyes. Rinse with water to remove.

Stop use and ask a doctor if rash occurs

Keep out of reach of children. If swallowed, get medical help or contact a Poison Control Center right away.

Directions

- apply liberally 15 minutes before sun exposure
- reapply at least every 2 hours
- use a water resistant sunscreen if swimming or sweating
- children under 6 months of age: Ask a doctor

Inactive ingredients

arachidyl alcohol, arachidyl glucoside, behenyl alcohol, bis-diglyceryl polyacyladipate-2, flavors, hydrogenated polyisobutene, isostearoyl hydrolyzed silk, mica, microcrystalline wax, mineral oil, ozokerite, panthenyl ethyl ether, paraffin, pentaerythrityl tetraethylhexanoate, petrolatum, phenoxyethanol, phenyl trimethicone, polybutene, PPG-5-Ceteth-20, saccharin, titanium dioxide, tocopheryl acetate

Other information

- protect the product in this container from excessive heat and direct sun

PRINCIPAL DISPLAY PANEL - 3.69g Cylinder Blister Pack

NDC 10157-9882-1
Blistex®
LIP PROTECTANT/SUNSCREEN

SILK &
SHINE®

Now!
More Silk
More Shine

Satiny Smooth Lips
Plus A Light Glossy Shine
SPF 15

Infused With Real Silk Extracts

NET WT. .13 oz (3.69g)